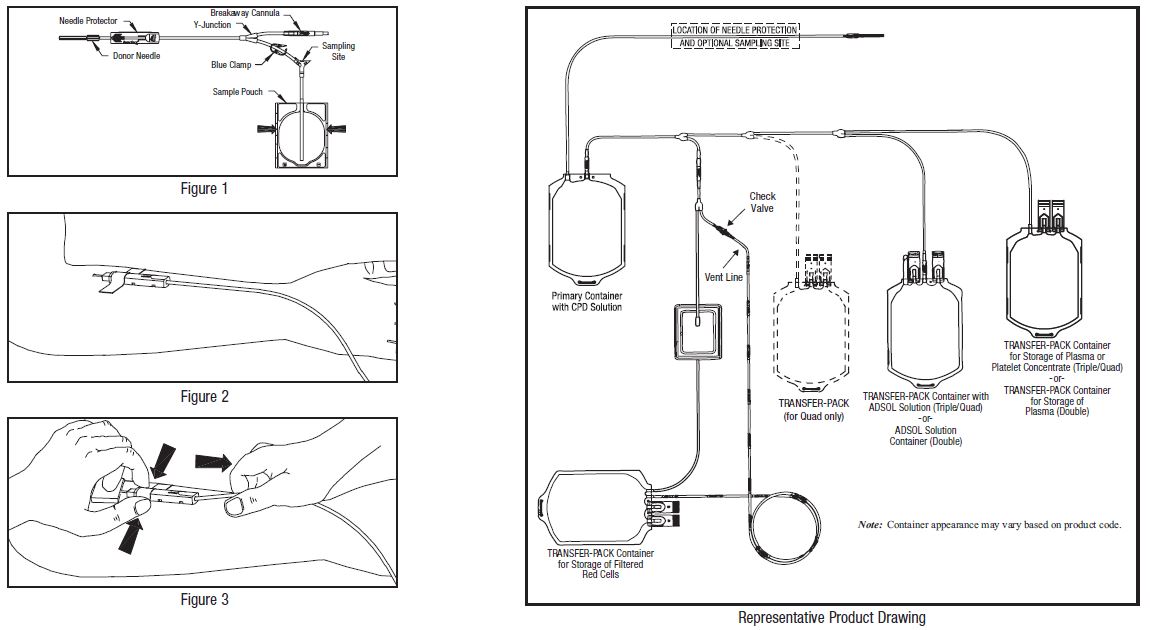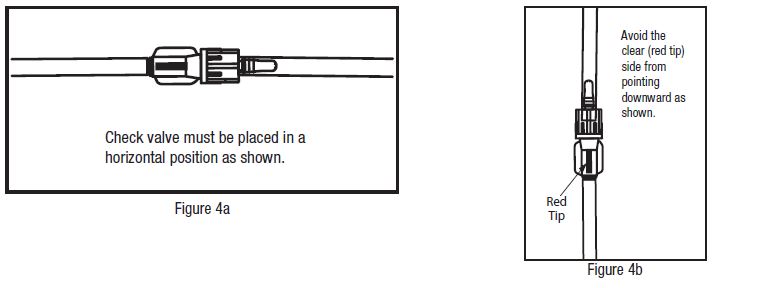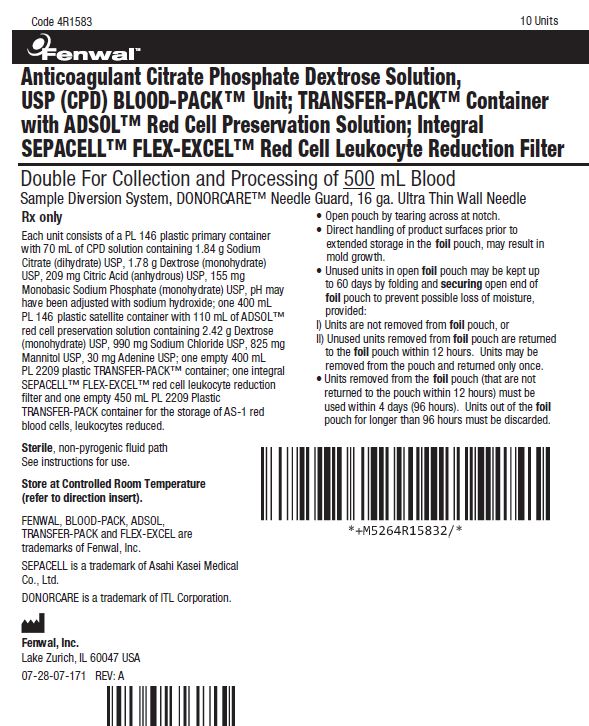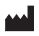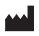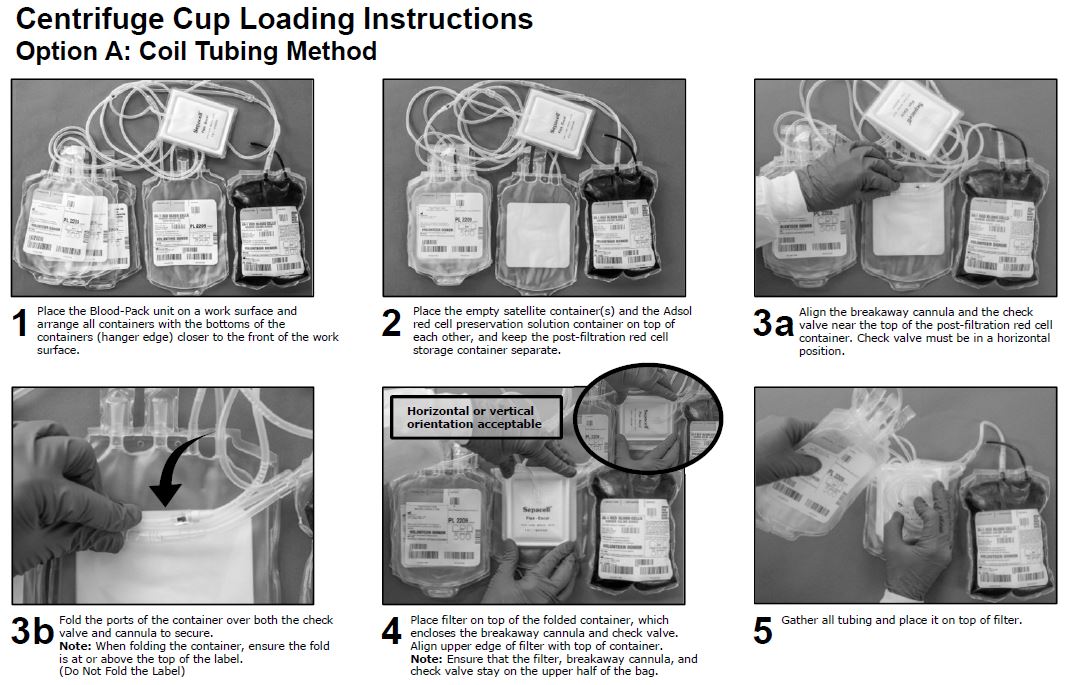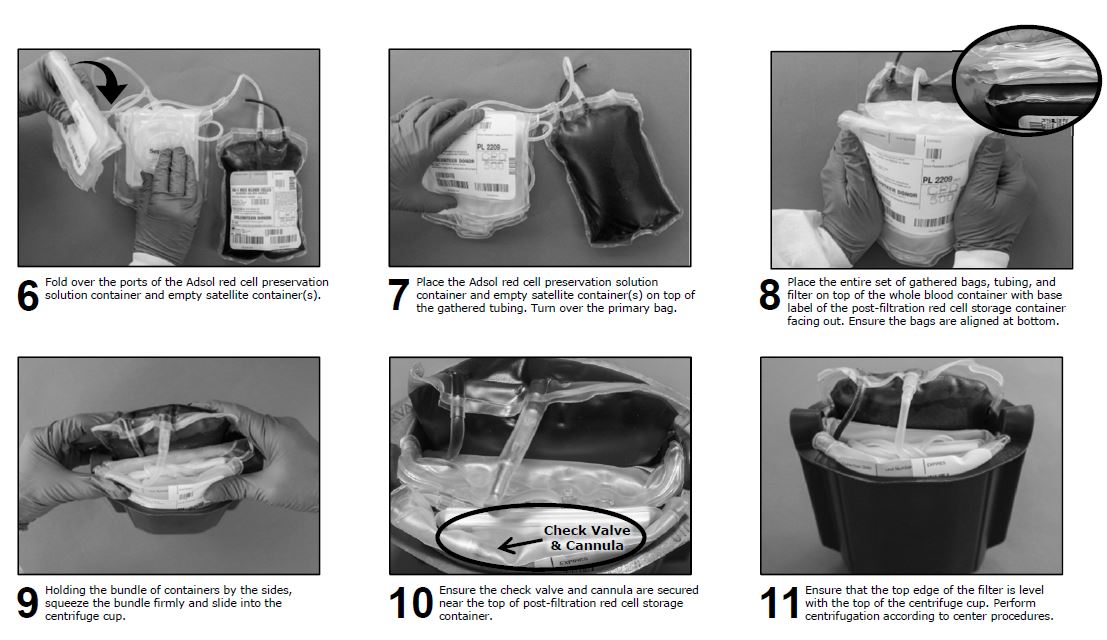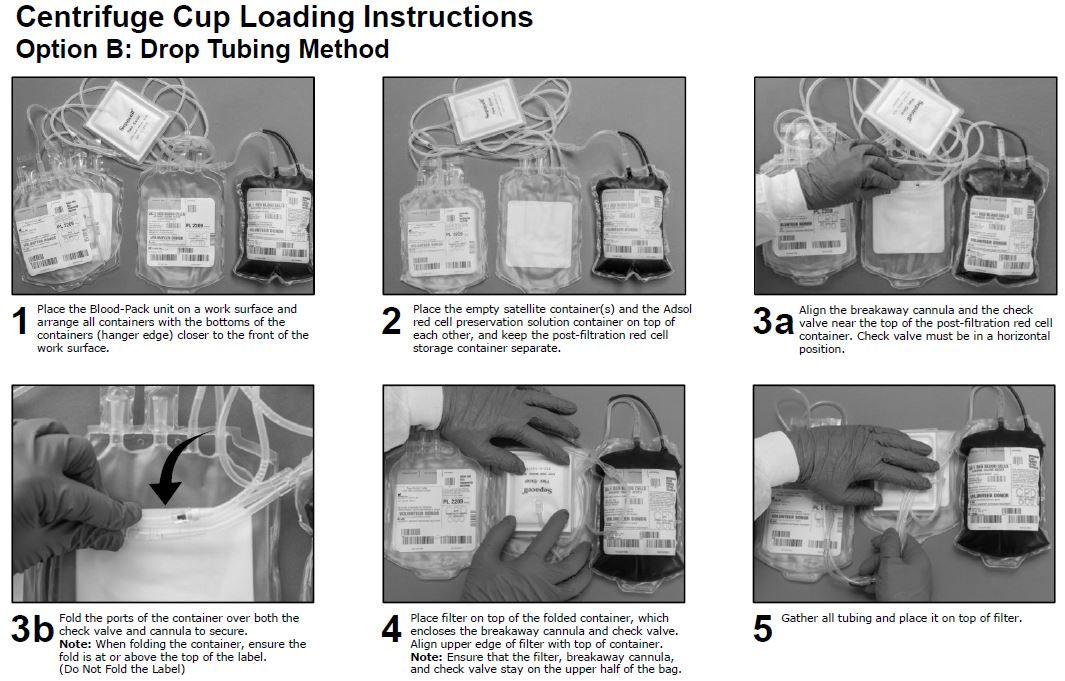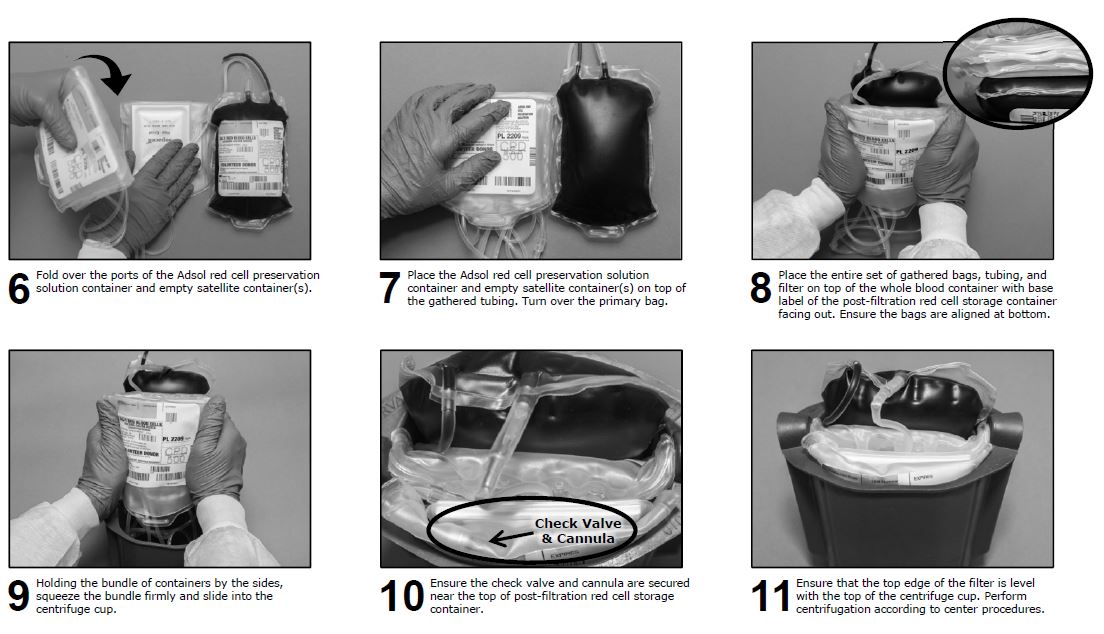 DRUG LABEL: ADSOL Red Cell Preservation Solution System in Plastic Container (PL 146 Plastic)
NDC: 0942-6477 | Form: KIT | Route: INTRAVENOUS
Manufacturer: Fenwal, Inc.
Category: prescription | Type: HUMAN PRESCRIPTION DRUG LABEL
Date: 20211201

ACTIVE INGREDIENTS: Trisodium Citrate Dihydrate 1.84 g/70 mL; Dextrose Monohydrate 1.78 g/70 mL; Anhydrous Citric Acid 209 mg/70 mL; Sodium Phosphate, Monobasic, Monohydrate 155 mg/70 mL; Dextrose Monohydrate 2.42 g/110 mL; Sodium Chloride 990 mg/110 mL; Mannitol 825 mg/110 mL; Adenine 30 mg/110 mL
INACTIVE INGREDIENTS: Sodium Hydroxide

BLOOD-PACK™ Unit with an Integral SEPACELL™ FLEX-EXCEL™ Leukocyte Reduction Filter Using CPD/ADSOL™ Red Cell Preservation Solution for Whole Blood Collection and Filtration of Red Blood Cells

Rx only
Contains Sample Diversion System for the collection of whole blood samples for laboratory testing. Also includes the DONORCARE™ Needle Guard.
Integral filter unit intended for leukocyte reduction of AS-1 red blood cells:
•At ambient temperature up to 8 hours after blood collection.
•At refrigerated temperature up to 3 days after blood collection if AS-1 red blood cells are prepared within 3 days after whole blood collection.
The leukocyte reduced red blood cells may then be stored for the maximum allowable dating period.
Instructions for Use
Collection Procedure:
Use aseptic technique.
Notes:
• If sample diversion system is not used, donor samples may be collected using an alternate method following standard procedures.
• Nominal tubing dimensions of product are 0.118" inner diameter x 0.025" wall thickness.
Precautions:
• Upon removal of BLOOD-PACK™ unit from the clear plastic overwrap, visually inspect the unit.
• Do not use the product if the in-line cannula is broken and/or anticoagulant is present in the sample pouch or in the tubing from the in-line cannula to the sample pouch and donor needle (see Figure 1). Note that condensation in the empty tubing of the BLOOD-PACK unit is expected as a result of the sterilization process.
• Do not use unless the solutions are clear.
1. Identify BLOOD-PACK unit using appropriate donor identification system.
2. Donor scale
• Adjust donor scale to desired collection weight.
• Position primary container on the donor scale as far as possible below donor arm.
3. Clamp donor tubing between the needle and Y-junction with hemostat. (This step can be performed prior to step 1 or 2.)
4. Visually inspect the tubing from the in-line cannula to the sample pouch and donor needle, as well as the sample pouch to reconfirm that there is no anticoagulant present.
Note: Ensure that the sample pouch remains below the donor's arm.
5. Follow blood center procedures, apply pressure to donor's arm and disinfect site of venipuncture.
6. Remove needle cover per instructions below:
• Holding the hub and cover near the tamper-evident seal, twist cover 1/4 turn to break seal.
• Remove needle cover, being careful not to drag the cover across the needle point.
7. Following blood center procedures, perform venipuncture, appropriately secure donor needle and/or tubing and release hemostat.
8. When good blood flow is established, slide the DONORCARE™ needle guard over the needle hub into the engaged position. Leave the front third of the needle hub exposed for access. Stabilize the front of the needle guard to arm with tape. (see Figure 2)
Note: In difficult collection conditions (e.g., slow blood flow), leave the needle guard disengaged behind the hub during collection. Engage the needle guard at the end of blood collection. Appropriately secure needle and/or tubing.
9. Allow the sample pouch to fill with blood according to center procedure. Monitor blood flow into sample pouch.
Notes:
• The sample pouch contains an average fill volume of approximately 53 mL with a maximum fill volume of approximately 60 mL when filled to capacity.
• If less blood sample volume is required, the flow to the sample pouch may be stopped prior to completely filling the pouch. For example, in order to target a fill volume of approximately 40 mL, fill to the level indicated by the arrows in Figure 1. Ensure the pouch is hanging vertically.
• The tube leading from the Y-junction to the sample pouch contains an additional volume of approximately 2 mL .
Precautions:
• Do not elevate or squeeze the sample pouch as this could cause blood to backflow from the sample pouch into the collection system.
• Once the sample pouch is filled to desired volume, complete steps 10 - 18 within approximately 4 minutes to avoid possible clot formation in the tubing and/or sample pouch.
10. Close the blue clamp on tubing between the Y-junction and the sample pouch.
11. Break the in-line cannula below the Y-junction in the donor tubing to the primary container allowing blood collection to proceed. To completely break the in-line cannula, grasp with both hands. Snap it at a 90° angle in one direction, and then bend it at a 90° angle in the opposite direction. Ensure the in-line cannula is completely broken and that the blood flows freely to the primary container.
Precaution: Failure to break the in-line cannula completely may result in restricted blood flow.
12. Following blood center procedures, mix blood and anticoagulant in the primary container immediately and at several intervals during collection.
13. Following blood center procedures, hermetically seal the tubing between the sampling site and the Y-junction to maintain sterility of the blood collection system prior to removing blood samples.
Warning:
• Do not proceed with the remaining steps until the tubing leading to the sample pouch is hermetically sealed between the sampling site and the Y-junction. To maintain the whole blood collection container as a closed system, the tubing between the sample pouch and Y-junction must be hermetically sealed prior to inserting the access device into the sampling site. Failure to do so may lead to contamination of the whole blood collection.
14. Insert the access device by pushing firmly into the sampling site until the membrane seal is penetrated.
Note: If the access device is assembled such that the outer barrel is screwed onto the Luer, make sure to rotate clockwise upon insertion to avoid barrel detaching from Luer.
15. Open the cap on the access device (if applicable). Hold access device so that the sample pouch hangs down.
16. Directly align the vacuum sample tube with the internal needle in the access device. Insert vacuum sample tube into device.
17. Allow vacuum sample tube to fill with blood then remove from the access device.
18. Repeat steps 16 and 17 until the desired number of vacuum sample tubes have been filled.
Notes:
• If the access device needs to be replaced, use a hemostat to clamp the tubing between the sampling site and the sample pouch. Then, grasp base of sampling site with one hand and pull the access device out with the other hand. Firmly insert the new access device. Remove hemostat and continue sampling.
• If the access device is assembled such that the outer barrel is screwed onto the Luer, make sure to rotate clockwise upon removal to avoid barrel detaching from Luer.
• The access device can only be replaced one time.
Precaution: When replacing access device, be careful to avoid contact with any blood droplets on the
Luer or sampling site. Discard used access device appropriately.
19. Collect the appropriate volume based on BLOOD-PACK unit used.
Note: The volume of anticoagulant is sufficient for the blood collection indicated on BLOOD-PACK unit ± 10%.
Precaution: Once the desired blood volume is collected, complete steps 20-24 within approximately 4 minutes to avoid possible clot formation in the tubing.
20. Release pressure on the donor’s arm. If appropriate, apply hemostat to donor tubing between the needle and the Y-junction.
21. Hermetically seal donor tubing between the in-line cannula and the primary container.
22. Withdrawal of Needle (see Figure 3)
Precaution: The needle guard must be held stationary while the needle is withdrawn into it.
a) Place folded sterile gauze over puncture site and hold in place with finger tip without exerting pressure.
b) Hold sides of needle guard near the front, between the index finger and thumb. Pull the tubing smoothly until the needle is locked into the needle guard.
c) Confirm the needle lock by:
• Listen for the 2nd “click” as the needle is drawn into the needle guard.
• Ensure the tubing cannot be pulled through the needle guard.
23. Remove and discard the sample diversion system and needle guard into an appropriate biohazardous waste container following established procedures.
Note: Step 24 may be performed prior to step 23 if desired.
24. If the donor tubing is not hermetically sealed directly above the primary container, then strip the blood from the remaining donor tubing into the primary container. Mix and allow tubing to refill; repeat once.
Component Preparation:
Notes:
• If a platelet concentrate is to be prepared, it should be separated within 8 hours after blood collection.
• Fresh frozen plasma should be separated from the red blood cells and placed in the freezer at -18°C or colder within 8 hours after blood collection.
• ADSOL™ red cell preservation solution should be added to the red blood cells immediately after the removal of plasma. Preparation of AS-1 red blood cells may vary depending on processing option selected:
a) Within 8 hours of blood collection if whole blood is held at ambient temperature.
b) Within 3 days of blood collection if whole blood is refrigerated.
25. At the appropriate time, prepare the BLOOD-PACK unit with Integral Filter for centrifugation.
26. Thoroughly mix the primary container end over end.
27. Load the BLOOD-PACK Unit into a centrifuge cup per the instructions on page 3 or 4.
Page 3 describes Option A, the coil tubing method of cup loading.
Page 4 describes Option B, the drop tubing method of cup loading.
Notes:
• This guide is one method for centrifuge cup loading and applies to all Flex-Excel configurations. The specific stacking order and methods may vary depending on the workstation setup, centrifuge equipment, and Standard Operating Procedures.
• It is important to pack the filter properly in the centrifugation cup to avoid damage to the filter during centrifugation.
• Check valve must be placed in a horizontal position (Figure 4a, page 2). Avoid the clear (red tip) side from pointing downward (Figure 4b, page 2). See step 3 on page 3 or 4.
• Do not place the filter, breakaway cannula or check valve in the lower half of the centrifuge cup.
See step 5 on page 3 or 4.
28. After loading the BLOOD-PACK Unit into the centrifuge cup, perform centrifugation according to center procedures.
29. Following centrifugation, remove containers from the centrifugation cup taking care not to disturb the red blood cell / plasma interface.
30. Place primary container in a plasma extractor and apply pressure. If applicable, clamp off tubing below Y-Junction leading to secondary TRANSFER-PACK™ container not to be filled with plasma. Open the cannula on the top of the primary container to transfer plasma into the empty TRANSFER-PACK container.
31. When the desired amount of plasma has been removed, clamp the tubing between the plasma container and the Y-connector closest to the plasma container and release pressure on the primary container.
32. Suspend the ADSOL red cell preservation solution container, open the cannula on the ADSOL solution container and drain the contents into the primary container of the CPD red blood cells. Clamp the ADSOL red cell preservation solution tubing.
33. Hermetically seal the tubing between the Y-connectors or above the plasma TRANSFER-PACK container.
Be careful to avoid fluid splatter.
34. Mix the ADSOL red cell preservation solution and red cells thoroughly.
Note: If the ADSOL red cell preservation solution is not added to the red cells, ensure appropriate labeling of the red cell container. The pre-filter container does not include tubing with segment numbers.
A CPD red cell without ADSOL red cell preservation solution may be stored between 1 and 6ºC up to 21 days after collection. The attached SEPACELL™ FLEX-EXCEL™ filter should not be used to leukoreduce a CPD red cell without ADSOL red cell preservation solution.
Filtration Procedure:
Precaution: Red blood cell products collected from certain donors may have extended filtration times and the potential for ineffective filtration and leukoreduction.
35. Mix unfiltered AS-1 red blood cells thoroughly. Invert the unfiltered AS-1 red blood cells and hang the filter set such that the filter remains vertical. To achieve maximum flow rate, allow the set to hang to full length.
Note: The storage container must remain below the level of the filter during filtration.
36. Inspect all tubing to ensure it hangs freely without kinks. If desired, a temporary clamp may be placed on the vent line, but must be removed prior to expelling air through the vent line.
37. Break the in-line cannula above the filter to start filtration.
Note: Manual or mechanical pressure should not be used to increase the flow rate through the filter.
Note: Tubing below the filter should not be stripped at any time during the filtration process.
Note: If filtration of red cells is initiated at ambient temperature, the filtration process can be completed at either ambient or refrigerated temperature prior to storing the red cells between 1 and 6°C.
However, for optimal filtration time, it is recommended to complete the filtration at ambient temperature.
38. As the filtered red cell storage container is filling, or when flow stops, clamp or pinch the tubing below the filter to occlude flow.
Note: While the check valve is designed to prevent blood flow from entering the vent line below the valve, blood may flow down and fill the valve.
39. Squeeze the filtered red cell storage container to expel air from the filtered red cell container through the vent line. Continue squeezing the filtered red cell container until the vent line segments and check valve are filled with blood as desired.
40. Remove the clamp or release the tubing below the filter to resume red cell flow through the filter. If desired, the temporary clamp may be replaced on the vent line immediately after removing the clamp below the filter. When filtration is complete, air can be observed in the inlet side of the filter.
Note: While the check valve is designed to prevent blood flow from entering the vent line below the valve, it is normal for air to pass through the valve and enter the vent line tubing. To avoid air from entering the vent line below the valve, the vent line may be clamped during this step, or blood may be expressed beyond the check valve during the air expel operation.
41. Hermetically seal and detach the tubing below the filter. Also, hermetically seal and detach the vent line between the one way valve and the top donor segment number.
42. Make segments from the vent line tubing and leave segments attached to the filtered red cell storage container. (QC samples may be prepared by thoroughly mixing the filtered red cells and stripping this tubing prior to sealing the segments.)
43. Store the AS-1 red blood cells, leukocytes reduced between 1 and 6°C.
44. Infuse the red cells within 42 days of collection.
Warning: Failure to achieve closed system processing conditions negates the extended storage claim and the red blood cell product must be transfused within 24 hours.

Store at Controlled Room Temperature.
USP Definition of “Controlled Room Temperature” United States Pharmacopeia, General Notices. United States Pharmacopeial Convention, Inc.
12601 Twinbrook Parkway, Rockville, MD

Fenwal, Inc.
Lake Zurich, IL 60047 USA
Made in USA
1-800-933-6925

Manufacturer
FENWAL, BLOOD-PACK, TRANSFER-PACK, ADSOL and FLEX-EXCEL are trademarks of Fenwal, Inc.
SEPACELL is a trademark of Asahi Kasei Medical Co., Ltd.
DONORCARE is a trademark of ITL Corporation.
© 2018 Fenwal, Inc. All rights reserved.
07-19-13-106 REV: A

PACKAGE/LABEL DISPLAY PANEL

Code 4R1583

10 Units

Fenwal™

Anticoagulant Citrate Phosphate Dextrose Solution, USP (CPD) BLOOD-PACK™ Unit; TRANSFER-PACK™ Container with ADSOL™ Red Cell Preservation Solution; Integral SEPACELL™ FLEX-EXCEL™ Red Cell Leukocyte Reduction Filter

Double For Collection and Processing of 500 mL Blood

Sample Diversion System, DONORCARE™ Needle Guard, 16 ga. Ultra Thin Wall Needle

Rx only

Each unit consists of a PL 146 Plastic primary container with 70 mL of CPD solution containing 1.84 g Sodium Citrate (dihydrate) USP, 1.78 g Dextrose (monohydrate) USP, 209 mg Citric Acid (anhydrous) USP, 155 mg Monobasic Sodium Phosphate (monohydrate) USP, pH may have been adjusted with sodium hydroxide; one 400 mL PL 146 plastic satellite container with 110 mL of ADSOL™ red cell preservation solution containing 2.42 g Dextrose (monohydrate) USP, 990 mg Sodium Chloride USP, 825 mg Mannitol USP, 30 mg Adenine USP; one empty 400 mL PL 2209 Plastic TRANSFER-PACK™ container; one integral SEPACELL™ FLEX-EXCEL™ red cell leukocyte reduction filter and one empty 450 mL PL 2209 Plastic TRANSFER-PACK container for the storage of AS-1 red blood cells, leukocytes reduced.

Sterile, non-pyrogenic fluid path.
See instructions for use.

Store at Controlled Room Temperature (refer to direction insert).

- Open pouch by tearing across at notch.
- Direct handling of product surfaces prior to extended storage in the foil pouch, may result in mold growth.
- Unused units in open foil pouch may be kept up to 60 days by folding and securing open end of foil pouch to prevent possible loss of moisture, provided:

I) Units are not removed from foil pouch, or

II)Unused units removed from foil pouch are returned to the foil pouch within 12 hours. Units may be removed from the pouch and returned only once.

- Units removed from the foil pouch (that are not returned to the pouch within 12 hours) must be used within 4 days (96 hours). Units out of the foil pouch for longer than 96 hours must be discarded

FENWAL, BLOOD-PACK, ADSOL, TRANSFER-PACK and FLEX-EXCEL are trademarks of Fenwal, Inc.
SEPACELL is a trademark of Asahi Kasei Medical Co., Ltd.
DONORCARE is a trademark of ITL Corporation.

Fenwal, Inc.
Lake Zurich, IL 60047 USA

Made in USA

07-28-07-171 REV: A